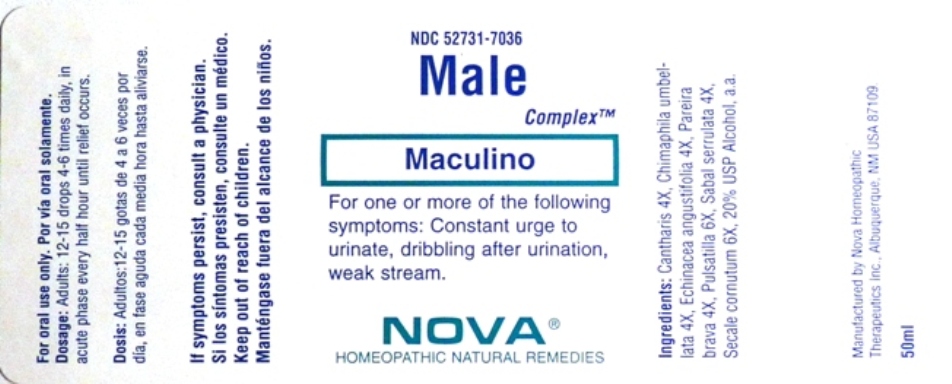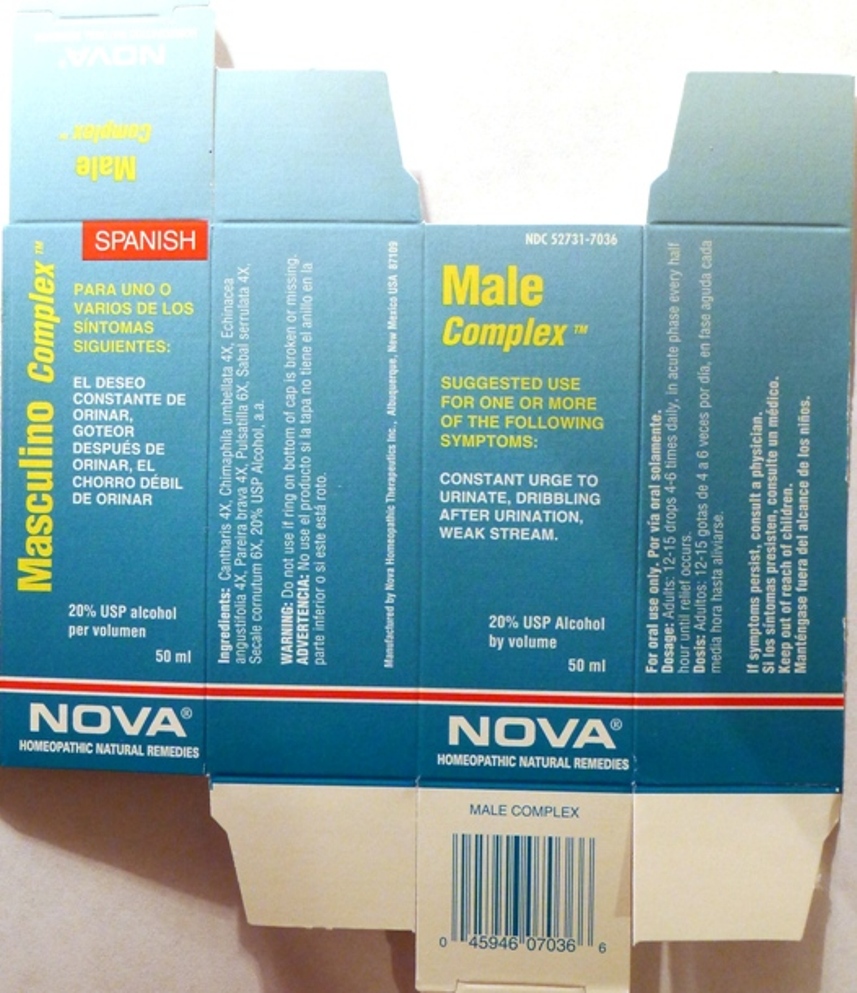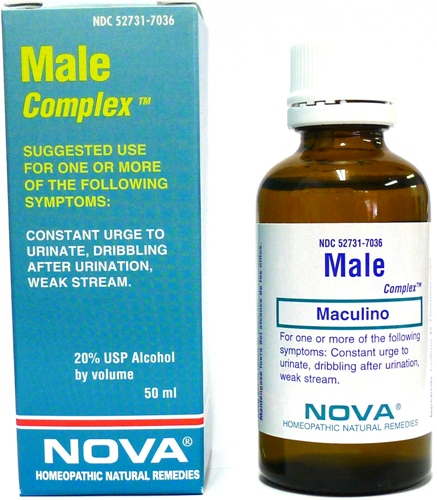 DRUG LABEL: Male Complex
NDC: 52731-7036 | Form: LIQUID
Manufacturer: Nova Homeopathic Therapeutics, Inc.
Category: homeopathic | Type: HUMAN OTC DRUG LABEL
Date: 20110601

ACTIVE INGREDIENTS: LYTTA VESICATORIA 4 [hp_X]/1 mL; CHIMAPHILA UMBELLATA 4 [hp_X]/1 mL; ECHINACEA ANGUSTIFOLIA 4 [hp_X]/1 mL; CHONDRODENDRON TOMENTOSUM ROOT 4 [hp_X]/1 mL; PULSATILLA VULGARIS 6 [hp_X]/1 mL; SAW PALMETTO 4 [hp_X]/1 mL; CLAVICEPS PURPUREA SCLEROTIUM 6 [hp_X]/1 mL
INACTIVE INGREDIENTS: ALCOHOL

Male Complex

Purpose:

Suggested use for one or more of the following symptoms:
Constant urge to urinate, dribbling after urination, weak stream.

Usage and Dosage:

For oral use only.

DOSAGE AND ADMINISTRATION

Adults:
In Acute Phase:
12-15 drops, every half hour until relief occurs
When Relief Occurs:
12-15 drops, 4-6 times per day

Warnings:

Keep out of reach of children.

WARNINGS

If symptoms persist, consult a physician.
Do not use if ring on bottom of cap is broken or missing.

Active Ingredients:

Cantharis 4x, Chimaphila umbellata 4x, Echinacea angustifolia 4x, Pareira brava 4x, Pulsatilla 6x, Sabal Serrulata 4x, Secale cornutum 6x

Inactive Ingredients:

Alcohol, 20% USP

QUESTIONS

Manufactured by Nova Homeopathic Therapeutics Inc., Albuquerque, New Mexico USA 87109
1-800-225-8094

PACKAGE LABEL

Male Complex Product

Male Complex Bottle Label

Male Complex Box